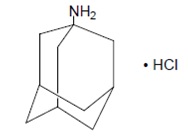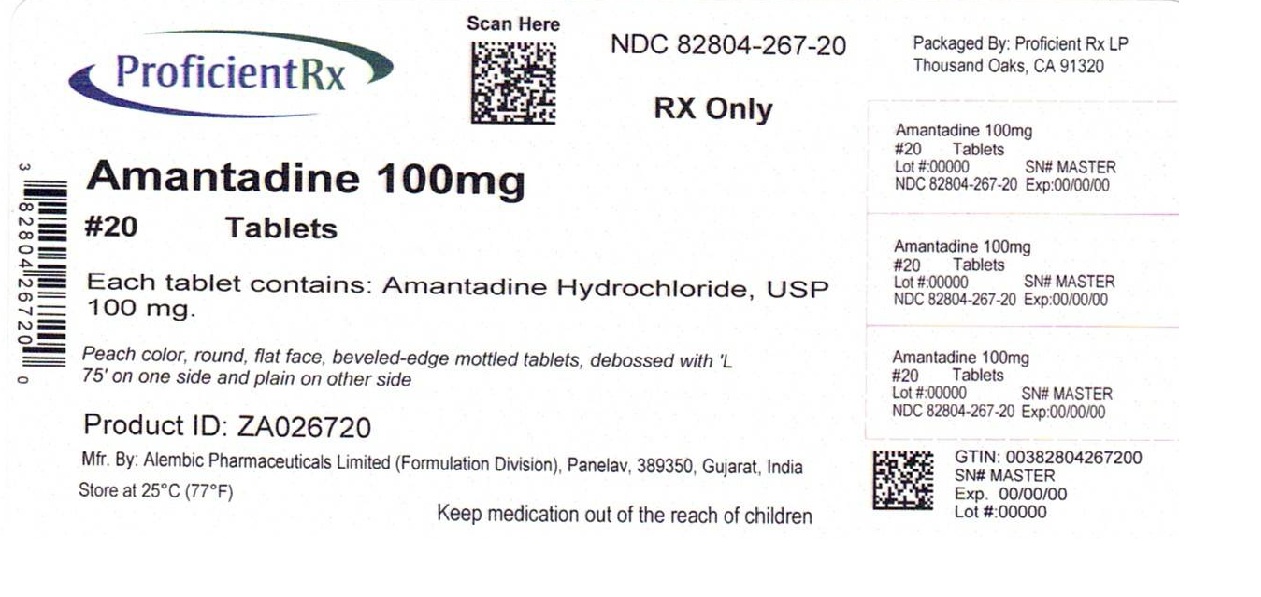 DRUG LABEL: Amantadine
NDC: 82804-267 | Form: TABLET
Manufacturer: Proficient Rx LP
Category: prescription | Type: HUMAN PRESCRIPTION DRUG LABEL
Date: 20260201

ACTIVE INGREDIENTS: AMANTADINE HYDROCHLORIDE 100 mg/1 1
INACTIVE INGREDIENTS: MICROCRYSTALLINE CELLULOSE; POVIDONE K30; POVIDONE K90; SODIUM STARCH GLYCOLATE TYPE A POTATO; SILICON DIOXIDE; MAGNESIUM STEARATE; FD&C YELLOW NO. 6

Amantadine Hydrochloride Tablets, USP
Rx only

DESCRIPTION

Amantadine hydrochloride, USP is designated generically as amantadine hydrochloride and chemically as 1-adamantanamine hydrochloride.

Amantadine hydrochloride, USP is a stable white or practically white crystalline powder, freely soluble in water, soluble in alcohol and in chloroform.
Amantadine hydrochloride, USP has pharmacological actions as both an anti-Parkinson and an antiviral drug.
Each tablet intended for oral administration contains 100 mg amantadine hydrochloride, USP and has the following inactive ingredients: microcrystalline cellulose, povidone K-30, povidone K-90, sodium starch glycolate, colloidal silicon dioxide, magnesium stearate and FD&C Yellow No. 6 Aluminium Lake.

CLINICAL PHARMACOLOGY

Pharmacodynamics
Mechanism of Action: Antiviral

The mechanism by which amantadine exerts its antiviral activity is not clearly understood. It appears to mainly prevent the release of infectious viral nucleic acid into the host cell by interfering with the function of the transmembrane domain of the viral M2 protein. In certain cases, amantadine is also known to prevent virus assembly during virus replication. It does not appear to interfere with the immunogenicity of inactivated influenza A virus vaccine.

Antiviral Activity

Amantadine inhibits the replication of influenza A virus isolates from each of the subtypes, i.e., H1N1, H2N2 and H3N2. It has very little or no activity against influenza B virus isolates. A quantitative relationship between the in vitro susceptibility of influenza A virus to amantadine and the clinical response to therapy has not been established in man. Sensitivity test results, expressed as the concentration of amantadine required to inhibit by 50% the growth of virus (ED50) in tissue culture vary greatly (from 0.1 μg/mL to 25 μg/mL) depending upon the assay protocol used, size of virus inoculum, isolates of influenza A virus strains tested, and the cell type used. Host cells in tissue culture readily tolerated amantadine up to a concentration of 100 μg/mL.

Drug Resistance

Influenza A variants with reduced in vitro sensitivity to amantadine have been isolated from epidemic strains in areas where adamantane derivatives are being used. Influenza viruses with reduced in vitro sensitivity have been shown to be transmissible and to cause typical influenza illness. The quantitative relationship between the in vitro sensitivity of influenza A variants to amantadine and the clinical response to therapy has not been established.

Mechanism of Action: Parkinson’s Disease

The mechanism of action of amantadine in the treatment of Parkinson’s disease and drug-induced extrapyramidal reactions is not known. Data from earlier animal studies suggest that amantadine hydrochloride may have direct and indirect effects on dopamine neurons. More recent studies have demonstrated that amantadine is a weak, non-competitive NMDA receptor antagonist (Ki = 10μM). Although amantadine has not been shown to possess direct anticholinergic activity in animal studies, clinically, it exhibits anticholinergic-like side effects such as dry mouth, urinary retention, and constipation.

Pharmacokinetics

Amantadine hydrochloride is well absorbed orally. Maximum plasma concentrations are directly related to dose for doses up to 200 mg/day. Doses above 200 mg/day may result in a greater than proportional increase in maximum plasma concentrations. It is primarily excreted unchanged in the urine by glomerular filtration and tubular secretion. Eight metabolites of amantadine have been identified in human urine. One metabolite, an N-acetylated compound, was quantified in human urine and accounted for 5 to 15% of the administered dose. Plasma acetylamantadine accounted for up to 80% of the concurrent amantadine plasma concentration in 5 of 12 healthy volunteers following the ingestion of a 200 mg dose of amantadine. Acetylamantadine was not detected in the plasma of the remaining seven volunteers. The contribution of this metabolite to efficacy or toxicity is not known.

There appears to be a relationship between plasma amantadine concentrations and toxicity. As concentration increases, toxicity seems to be more prevalent, however, absolute values of amantadine concentrations associated with adverse effects have not been fully defined.

Amantadine pharmacokinetics were determined in 24 normal adult male volunteers after the oral administration of a single amantadine hydrochloride 100 mg soft gel capsule. The mean ± SD maximum plasma concentration was 0.22 ± 0.03 μg/mL (range: 0.18 to 0.32 μg/mL). The time to peak concentration was 3.3 ± 1.5 hours (range: 1.5 to 8 hours). The apparent oral clearance was 0.28 ± 0.11 L/hr/kg (range: 0.14 to 0.62 L/hr/kg). The half-life was 17 ± 4 hours (range: 10 to 25 hours). Across other studies, amantadine plasma half-life has averaged 16 ± 6 hours (range: 9 to 31 hours) in 19 healthy volunteers.

After oral administration of a single dose of 100 mg amantadine syrup to five healthy volunteers, the mean ± SD maximum plasma concentration Cmax was 0.24 ± 0.04 μg/mL and ranged from 0.18 to 0.28 μg/mL. After 15 days of amantadine 100 mg b.i.d., the Cmax was 0.47 ± 0.11 μg/mL in four of the five volunteers. The administration of amantadine tablets as a 200 mg single dose to 6 healthy subjects resulted in a Cmax of 0.51 ± 0.14 μg/mL. Across studies, the time to Cmax (Tmax) averaged about 2 to 4 hours.

Plasma amantadine clearance ranged from 0.2 to 0.3 L/hr/kg after the administration of 5 mg to 25 mg intravenous doses of amantadine to 15 healthy volunteers.

In six healthy volunteers, the ratio of amantadine renal clearance to apparent oral plasma clearance was 0.79 ± 0.17 (mean ± SD).

The volume of distribution determined after the intravenous administration of amantadine to 15 healthy subjects was 3 to 8 L/kg, suggesting tissue binding. Amantadine, after single oral 200 mg doses to 6 healthy young subjects and to 6 healthy elderly subjects has been found in nasal mucus at mean ± SD concentrations of 0.15 ± 0.16, 0.28 ± 0.26, and 0.39 ± 0.34 μg/g at 1, 4, and 8 hours after dosing, respectively. These concentrations represented 31 ± 33%, 59 ± 61%, and 95 ± 86% of the corresponding plasma amantadine concentrations. Amantadine is approximately 67% bound to plasma proteins over a concentration range of 0.1 to 2 μg/mL. Following the administration of amantadine 100 mg as a single dose, the mean ± SD red blood cell to plasma ratio ranged from 2.7 ± 0.5 in 6 healthy subjects to 1.4 ± 0.2 in 8 patients with renal insufficiency.

The apparent oral plasma clearance of amantadine is reduced and the plasma half-life and plasma concentrations are increased in healthy elderly individuals age 60 and older. After single dose administration of 25 to 75 mg to 7 healthy, elderly male volunteers, the apparent plasma clearance of amantadine was 0.1 ± 0.04 L/hr/kg (range 0.06 to 0.17 L/hr/kg) and the half-life was 29 ± 7 hours (range 20 to 41 hours). Whether these changes are due to decline in renal function or other age related factors is not known.

In a study of young healthy subjects (n=20), mean renal clearance of amantadine, normalized for body mass index, was 1.5 fold higher in males compared to females (p<0.032).

Compared with otherwise healthy adult individuals, the clearance of amantadine is significantly reduced in adult patients with renal insufficiency. The elimination half-life increases two to three fold or greater when creatinine clearance is less than 40 mL/min/1.73 m^2 and averages eight days in patients on chronic maintenance hemodialysis. Amantadine is removed in negligible amounts by hemodialysis.

The pH of the urine has been reported to influence the excretion rate of amantadine hydrochloride. Since the excretion rate of amantadine hydrochloride increases rapidly when the urine is acidic, the administration of urine acidifying drugs may increase the elimination of the drug from the body.

INDICATIONS AND USAGE

Amantadine hydrochloride tablets are indicated for the prophylaxis and treatment of signs and symptoms of infection caused by various strains of influenza A virus. Amantadine hydrochloride tablets are also indicated in the treatment of parkinsonism and drug-induced extrapyramidal reactions.

Influenza A Prophylaxis

Amantadine hydrochloride tablets are indicated for chemoprophylaxis against signs and symptoms of influenza A virus infection. Because amantadine hydrochloride tablets do not completely prevent the host immune response to influenza A infection, individuals who take this drug may still develop immune responses to natural disease or vaccination and may be protected when later exposed to antigenically related viruses. Following vaccination during an influenza A outbreak, amantadine hydrochloride tablets prophylaxis should be considered for the 2- to 4-week time period required to develop an antibody response.

Influenza A Treatment

Amantadine hydrochloride tablets are also indicated in the treatment of uncomplicated respiratory tract illness caused by influenza A virus strains especially when administered early in the course of illness. There are no well-controlled clinical studies demonstrating that treatment with amantadine hydrochloride tablets will avoid the development of influenza A virus pneumonitis or other complications in high risk patients.

There is no clinical evidence indicating that amantadine hydrochloride tablets are effective in the prophylaxis or treatment of viral respiratory tract illnesses other than those caused by influenza A virus strains.

The following points should be considered before initiating treatment or prophylaxis with amantadine hydrochloride tablets:

- Amantadine hydrochloride tablets are not a substitute for early vaccination on an annual basis as recommended by the Centers for Disease Control and Prevention Advisory Committee on Immunization Practices.
- Influenza viruses change over time. Emergence of resistance mutations could decrease drug effectiveness. Other factors (for example, changes in viral virulence) might also diminish clinical benefit of antiviral drugs. Prescribers should consider available information on influenza drug susceptibility patterns and treatment effects when deciding whether to use amantadine hydrochloride tablets.

Parkinson’s Disease/Syndrome

Amantadine hydrochloride tablets are indicated in the treatment of idiopathic Parkinson’s disease (Paralysis Agitans), postencephalitic parkinsonism, and symptomatic parkinsonism which may follow injury to the nervous system by carbon monoxide intoxication. It is indicated in those elderly patients believed to develop parkinsonism in association with cerebral arteriosclerosis. In the treatment of Parkinson’s disease, amantadine hydrochloride tablets are less effective than levodopa, (-)-3-(3,4- dihydroxyphenyl)-L-alanine, and its efficacy in comparison with the anticholinergic antiparkinson drugs has not yet been established.

Drug-Induced Extrapyramidal Reactions

Amantadine hydrochloride tablets are indicated in the treatment of drug-induced extrapyramidal reactions. Although anticholinergic-type side effects have been noted with amantadine hydrochloride tablets when used in patients with drug-induced extrapyramidal reactions, there is a lower incidence of these side effects than that observed with the anticholinergic antiparkinson drugs.

CONTRAINDICATIONS

Amantadine hydrochloride tablets are contraindicated in patients with known hypersensitivity to amantadine hydrochloride or to any of the other ingredients in amantadine hydrochloride tablets.

WARNINGS

Deaths

Deaths have been reported from overdose with amantadine hydrochloride. The lowest reported acute lethal dose was 1 gram. Acute toxicity may be attributable to the anticholinergic effects of amantadine. Drug overdose has resulted in cardiac, respiratory, renal or central nervous system toxicity. Cardiac dysfunction includes arrhythmia, tachycardia and hypertension (see OVERDOSAGE).
Deaths due to drug accumulation (overdosage) have been reported in patients with renal impairment, who were prescribed higher than recommended doses of Amantadine Hydrochloride for their level of renal function (see DOSAGE AND ADMINISTRATION; Dosage For Impaired Renal Function and OVERDOSAGE).

Suicide Attempts

Suicide attempts, some of which have been fatal, have been reported in patients treated with amantadine hydrochloride, many of whom received short courses for influenza treatment or prophylaxis. The incidence of suicide attempts is not known and the pathophysiologic mechanism is not understood. Suicide attempts and suicidal ideation have been reported in patients with and without prior history of psychiatric illness. Amantadine hydrochloride can exacerbate mental problems in patients with a history of psychiatric disorders or substance abuse. Patients who attempt suicide may exhibit abnormal mental states which include disorientation, confusion, depression, personality changes, agitation, aggressive behavior, hallucinations, paranoia, other psychotic reactions, and somnolence or insomnia. Because of the possibility of serious adverse effects, caution should be observed when prescribing amantadine hydrochloride tablets to patients being treated with drugs having CNS effects, or for whom the potential risks outweigh the benefit of treatment.

CNS Effects

Patients with a history of epilepsy or other “seizures” should be observed closely for possible increased seizure activity.

Patients receiving amantadine hydrochloride tablets who note central nervous system effects or blurring of vision should be cautioned against driving or working in situations where alertness and adequate motor coordination are important.

Other

Patients with a history of congestive heart failure or peripheral edema should be followed closely as there are patients who developed congestive heart failure while receiving amantadine hydrochloride tablets.

Patients with Parkinson’s disease improving on amantadine hydrochloride tablets should resume normal activities gradually and cautiously, consistent with other medical considerations, such as the presence of osteoporosis or phlebothrombosis.

Because amantadine hydrochloride tablets have anticholinergic effects and may cause mydriasis, it should not be given to patients with untreated angle closure glaucoma.

Corneal Edema

Corneal edema has been reported in patients taking amantadine. Symptoms include sudden onset of blurry vision, or progressive vision loss, with or without eye pain. Corneal involvement is usually bilateral. Onset can occur from a few weeks to several years after starting amantadine. Resolution of symptoms typically begins within weeks of amantadine cessation. However, corneal grafts have been required in some patients when the condition is not recognized. Permanent damage can occur if amantadine is continued. Ask patients if their vision has changed and obtain ophthalmologic examinations to rule out corneal edema should vision changes occur after initiation of therapy with amantadine. If corneal edema occurs, taper and discontinue amantadine [see Dosage and Administration].

PRECAUTIONS

Amantadine hydrochloride should not be discontinued abruptly in patients with Parkinson’s disease since a few patients have experienced a parkinsonian crisis, i.e., a sudden marked clinical deterioration, when this medication was suddenly stopped. The dose of anticholinergic drugs or of amantadine hydrochloride should be reduced if atropine-like effects appear when these drugs are used concurrently. Abrupt discontinuation may also precipitate delirium, agitation, delusions, hallucinations, paranoid reaction, stupor, anxiety, depression and slurred speech.

Neuroleptic Malignant Syndrome (NMS)

Sporadic cases of possible Neuroleptic Malignant Syndrome (NMS) have been reported in association with dose reduction or withdrawal of amantadine hydrochloride therapy. Therefore, patients should be observed carefully when the dosage of amantadine hydrochloride is reduced abruptly or discontinued, especially if the patient is receiving neuroleptics.

NMS is an uncommon but life-threatening syndrome characterized by fever or hyperthermia; neurologic findings including muscle rigidity, involuntary movements, altered consciousness; mental status changes; other disturbances such as autonomic dysfunction, tachycardia, tachypnea, hyper- or hypotension; laboratory findings such as creatine phosphokinase elevation, leukocytosis, myoglobinuria, and increased serum myoglobin.

The early diagnosis of this condition is important for the appropriate management of these patients. Considering NMS as a possible diagnosis and ruling out other acute illnesses (e.g., pneumonia, systemic infection, etc.) is essential. This may be especially complex if the clinical presentation includes both serious medical illness and untreated or inadequately treated extrapyramidal signs and symptoms (EPS). Other important considerations in the differential diagnosis include central anticholinergic toxicity, heat stroke, drug fever and primary central nervous system (CNS) pathology.

The management of NMS should include: 1) intensive symptomatic treatment and medical monitoring, and 2) treatment of any concomitant serious medical problems for which specific treatments are available. Dopamine agonists, such as bromocriptine, and muscle relaxants, such as dantrolene are often used in the treatment of NMS, however, their effectiveness has not been demonstrated in controlled studies.

Renal disease

Because amantadine hydrochloride is mainly excreted in the urine, it accumulates in the plasma and in the body when renal function declines. Thus, the dose of amantadine hydrochloride should be reduced in patients with renal impairment and in individuals who are 65 years of age or older (see DOSAGE AND ADMINISTRATION; Dosage for Impaired Renal Function).

Liver disease

Care should be exercised when administering amantadine hydrochloride to patients with liver disease. Rare instances of reversible elevation of liver enzymes have been reported in patients receiving amantadine hydrochloride, though a specific relationship between the drug and such changes has not been established.

Impulse Control/Compulsive Behaviors
Postmarketing reports suggest that patients treated with anti- Parkinson medications can experience intense urges to gamble, increased sexual urges, intense urges to spend money uncontrollably, and other intense urges. Patients may be unable to control these urges while taking one or more of the medications that are generally used for the treatment of Parkinson’s disease and that increase central dopaminergic tone, including amantadine hydrochloride. In some cases, although not all, these urges were reported to have stopped when the dose was reduced or the medication was discontinued. Because patients may not recognize these behaviors as abnormal it is important for prescribers to specifically ask patients or their caregivers about the development of new or increased gambling urges, sexual urges, uncontrolled spending or other urges while being treated with amantadine hydrochloride. Physicians should consider dose reduction or stopping the medication if a patient develops such urges while taking amantadine hydrochloride.

Melanoma

Epidemiological studies have shown that patients with Parkinson’s disease have a higher risk (2- to approximately 6-fold higher) of developing melanoma than the general population. Whether the increased risk observed was due to Parkinson’s disease or other factors, such as drugs used to treat Parkinson’s disease, is unclear.

For the reasons stated above, patients and providers are advised to monitor for melanomas frequently and on a regular basis when using amantadine hydrochloride tablets for any indication. Ideally, periodic skin examinations should be performed by appropriately qualified individuals (e.g., dermatologists).

Other

The dose of amantadine hydrochloride may need careful adjustment in patients with congestive heart failure, peripheral edema, or orthostatic hypotension. Care should be exercised when administering amantadine hydrochloride to patients with a history of recurrent eczematoid rash, or to patients with psychosis or severe psychoneurosis not controlled by chemotherapeutic agents.

Serious bacterial infections may begin with influenza-like symptoms or may coexist with or occur as complications during the course of influenza. Amantadine hydrochloride has not been shown to prevent such complications.

Information for Patients

Patients should be advised of the following information:

Blurry vision, eye pain, loss of vision, and/or impaired mental acuity may occur.

Gradually increase physical activity as the symptoms of Parkinson’s disease improve.

Avoid excessive alcohol usage, since it may increase the potential for CNS effects such as dizziness, confusion, lightheadedness and orthostatic hypotension.

Avoid getting up suddenly from a sitting or lying position. If dizziness or lightheadedness occurs, notify physician.

Notify physician if mood/mental changes, swelling of extremities, difficulty urinating and/or shortness of breath occur.

Do not take more medication than prescribed because of the risk of overdose. If there is no improvement in a few days, or if medication appears less effective after a few weeks, discuss with a physician.

Consult physician before discontinuing medication.

Seek medical attention immediately if it is suspected that an overdose of medication has been taken.

Drug Interactions

Careful observation is required when amantadine hydrochloride is administered concurrently with central nervous system stimulants.

Agents with anticholinergic properties may potentiate the anticholinergic-like side effects of amantadine.

Coadministration of thioridazine has been reported to worsen the tremor in elderly patients with Parkinson’s disease, however, it is not known if other phenothiazines produce a similar response. Coadministration of Dyazide (triamterene/hydrochlorothiazide) resulted in a higher plasma amantadine concentration in a 61-year-old man receiving amantadine hydrochloride 100 mg TID for Parkinson’s disease.^1 It is not known which of the components of Dyazide contributed to the observation or if related drugs produce a similar response.

Coadministration of quinine or quinidine with amantadine was shown to reduce the renal clearance of amantadine by about 30%.

The concurrent use of amantadine hydrochloride with live attenuated influenza vaccine (LAIV) intranasal has not been evaluated. However, because of the potential for interference between these products, LAIV should not be administered within 2 weeks before or 48 hours after administration of amantadine hydrochloride, unless medically indicated. The concern about possible interference arises from the potential for antiviral drugs to inhibit replication of live vaccine virus. Trivalent inactivated influenza vaccine can be administered at any time relative to use of amantadine hydrochloride.

Carcinogenesis and Mutagenesis

Long-term in vivo animal studies designed to evaluate the carcinogenic potential of amantadine hydrochloride have not been performed. In several in vitro assays for gene mutation, amantadine hydrochloride did not increase the number of spontaneously observed mutations in four strains of Salmonella typhimurium (Ames Test) or in a mammalian cell line (Chinese Hamster Ovary cells) when incubations were performed either with or without a liver metabolic activation extract. Further, there was no evidence of chromosome damage observed in an in vitro test using freshly derived and stimulated human peripheral blood lymphocytes (with and without metabolic activation) or in an in vivo mouse bone marrow micronucleus test (140 to 550 mg/kg; estimated human equivalent doses of 11.7 to 45.8 mg/kg based on body surface area conversion).

Impairment of Fertility

The effect of amantadine on fertility has not been adequately tested, that is, in a study conducted under Good Laboratory Practice (GLP) and according to current recommended methodology. In a three litter, non-GLP, reproduction study in rats, amantadine hydrochloride at a dose of 32 mg/kg/day (equal to the maximum recommended human dose on a mg/m^2 basis) administered to both males and females slightly impaired fertility. There were no effects on fertility at a dose level of 10 mg/kg/day (or 0.3 times the maximum recommended human dose on a mg/m^2 basis); intermediate doses were not tested.

Failed fertility has been reported during human in vitro fertilization (IVF) when the sperm donor ingested amantadine 2 weeks prior to, and during the IVF cycle.

Pregnancy

The effect of amantadine on embryofetal and peri-postnatal development has not been adequately tested, that is, in studies conducted under Good Laboratory Practice (GLP) and according to current recommended methodology. However, in two non-GLP studies in rats in which females were dosed from 5 days prior to mating to Day 6 of gestation or on Days 7 to 14 of gestation, amantadine hydrochloride produced increases in embryonic death at an oral dose of 100 mg/kg (or 3 times the maximum recommended human dose on a mg/m^2 basis). In the non-GLP rat study in which females were dosed on Days 7 to14 of gestation, there was a marked increase in severe visceral and skeletal malformations at oral doses of 50 and 100 mg/kg (or 1.5 and 3 times, respectively, the maximum recommended human dose on a mg/m^2 basis). The no-effect dose for teratogenicity was 37 mg/kg (equal to the maximum recommended human dose on a mg/m^2 basis). The safety margins reported may not accurately reflect the risk considering the questionable quality of the study on which they are based. There are no adequate and well-controlled studies in pregnant women. Human data regarding teratogenicity after maternal use of amantadine is scarce. Tetralogy of Fallot and tibial hemimelia (normal karyotype) occurred in an infant exposed to amantadine during the first trimester of pregnancy (100 mg P.O. for 7 days during the 6th and 7th week of gestation). Cardiovascular maldevelopment (single ventricle with pulmonary atresia) was associated with maternal exposure to amantadine (100 mg/d) administered during the first 2 weeks of pregnancy. Amantadine hydrochloride should be used during pregnancy only if the potential benefit justifies the potential risk to the embryo or fetus.

Nursing Mothers

Amantadine hydrochloride is excreted in human milk. Use is not recommended in nursing mothers.

Pediatric Use

The safety and efficacy of amantadine hydrochloride in newborn infants and infants below the age of 1 year have not been established.

Usage in the Elderly

Because amantadine hydrochloride is primarily excreted in the urine, it accumulates in the plasma and in the body when renal function declines. Thus, the dose of amantadine hydrochloride should be reduced in patients with renal impairment and in individuals who are 65 years of age or older. The dose of amantadine hydrochloride may need reduction in patients with congestive heart failure, peripheral edema, or orthostatic hypotension (see DOSAGE AND ADMINISTRATION).

ADVERSE REACTIONS

The adverse reactions reported most frequently at the recommended dose of amantadine hydrochloride (5 to 10%) are: nausea, dizziness (lightheadedness), and insomnia.

Less frequently (1 to 5%) reported adverse reactions are: depression, anxiety and irritability, hallucinations, confusion, anorexia, dry mouth, constipation, ataxia, livedo reticularis, peripheral edema, orthostatic hypotension, headache, somnolence, nervousness, dream abnormality, agitation, dry nose, diarrhea and fatigue.

Infrequently (0.1 to 1%) occurring adverse reactions are: congestive heart failure, psychosis, urinary retention, dyspnea, skin rash, vomiting, weakness, slurred speech, euphoria, thinking abnormality, amnesia, hyperkinesia, hypertension, decreased libido, and visual disturbance, including punctate subepithelial or other corneal opacity, corneal edema, decreased visual acuity, sensitivity to light, and optic nerve palsy.

Rare (less than 0.1%) occurring adverse reactions are: instances of convulsion, leukopenia, neutropenia, eczematoid dermatitis, oculogyric episodes, suicidal attempt, suicide, and suicidal ideation (see WARNINGS).

Other adverse reactions reported during postmarketing experience with amantadine hydrochloride usage include:

Nervous System/Psychiatric - coma, stupor, delirium, hypokinesia, hypertonia, delusions, aggressive behavior, paranoid reaction, manic reaction, involuntary muscle contractions, gait abnormalities, paresthesia, EEG changes, and tremor. Abrupt discontinuation may also precipitate delirium, agitation, delusions, hallucinations, paranoid reaction, stupor, anxiety, depression and slurred speech;

Cardiovascular - cardiac arrest, arrhythmias including malignant arrhythmias, hypotension, and tachycardia;

Respiratory - acute respiratory failure, pulmonary edema, and tachypnea;

Gastrointestinal - dysphagia;

Hematologic - leukocytosis; agranulocytosis

Special Senses - keratitis, mydriasis, and corneal edema;

Skin and Appendages - pruritus and diaphoresis;

Miscellaneous - neuroleptic malignant syndrome (see WARNINGS), allergic reactions including anaphylactic reactions, edema and fever.

Laboratory Test - elevated: CPK, BUN, serum creatinine, alkaline phosphatase, LDH, bilirubin, GGT, SGOT, and SGPT.

To report SUSPECTED ADVERSE REACTIONS, contact Alembic Pharmaceuticals Limited at 1-866-210-9797 or FDA at 1-800-FDA-1088 or www.fda.gov/medwatch.

OVERDOSAGE

Deaths have been reported from overdose with amantadine hydrochloride. The lowest reported acute lethal dose was 1 gram. Because some patients have attempted suicide by overdosing with amantadine, prescriptions should be written for the smallest quantity consistent with good patient management.

Acute toxicity may be attributable to the anticholinergic effects of amantadine. Drug overdose has resulted in cardiac, respiratory, renal or central nervous system toxicity. Cardiac dysfunction includes arrhythmia, tachycardia and hypertension. Pulmonary edema and respiratory distress (including adult respiratory distress syndrome - ARDS) have been reported; renal dysfunction including increased BUN, decreased creatinine clearance and renal insufficiency can occur. Central nervous system effects that have been reported include insomnia, anxiety, agitation, aggressive behavior, hypertonia, hyperkinesia, ataxia, gait abnormality, tremor, confusion, disorientation, depersonalization, fear, delirium, hallucinations, psychotic reactions, lethargy, somnolence and coma. Seizures may be exacerbated in patients with prior history of seizure disorders. Hyperthermia has also been observed in cases where a drug overdose has occurred.

There is no specific antidote for an overdose of amantadine hydrochloride. However, slowly administered intravenous physostigmine in 1 and 2 mg doses in an adult^2 at 1- to 2-hour intervals and 0.5 mg doses in a child^3 at 5- to 10-minute intervals up to a maximum of 2 mg/hour have been reported to be effective in the control of central nervous system toxicity caused by amantadine hydrochloride. For acute overdosing, general supportive measures should be employed along with immediate gastric lavage or induction of emesis. Fluids should be forced, and if necessary, given intravenously. The pH of the urine has been reported to influence the excretion rate of amantadine hydrochloride. Since the excretion rate of amantadine hydrochloride increases rapidly when the urine is acidic, the administration of urine acidifying drugs may increase the elimination of the drug from the body. The blood pressure, pulse, respiration and temperature should be monitored. The patient should be observed for hyperactivity and convulsions; if required, sedation, and anticonvulsant therapy should be administered. The patient should be observed for the possible development of arrhythmias and hypotension; if required, appropriate antiarrhythmic and antihypotensive therapy should be given. Electrocardiographic monitoring may be required after ingestion, since malignant tachyarrhythmias can appear after overdose.

Care should be exercised when administering adrenergic agents, such as isoproterenol, to patients with a amantadine hydrochloride overdose, since the dopaminergic activity of amantadine hydrochloride has been reported to induce malignant arrhythmias.

The blood electrolytes, urine pH and urinary output should be monitored. If there is no record of recent voiding, catheterization should be done.

DOSAGE AND ADMINISTRATION

The dose of amantadine hydrochloride tablets may need reduction in patients with congestive heart failure, peripheral edema, orthostatic hypotension, or impaired renal function (see Dosage for Impaired Renal Function).

Dosage for Prophylaxis and Treatment of Uncomplicated Influenza A Virus Illness

Adult

The adult daily dosage of amantadine hydrochloride tablet is 200 mg; two 100 mg tablets as a single daily dose. The daily dosage may be split into one tablet of 100 mg twice a day. If central nervous system effects develop in once-a-day dosage, a split dosage schedule may reduce such complaints. In persons 65 years of age or older, the daily dosage of amantadine hydrochloride tablet is 100 mg.

A 100 mg daily dose has also been shown in experimental challenge studies to be effective as prophylaxis in healthy adults who are not at high risk for influenza-related complications. However, it has not been demonstrated that a 100 mg daily dose is as effective as a 200 mg daily dose for prophylaxis, nor has the 100 mg daily dose been studied in the treatment of acute influenza illness. In recent clinical trials, the incidence of central nervous system (CNS) side effects associated with the 100 mg daily dose was at or near the level of placebo. The 100 mg dose is recommended for persons who have demonstrated intolerance to 200 mg of amantadine hydrochloride tablets daily because of CNS or other toxicities.

Pediatric Patients:

1 yr. to 9 yrs. of age

The total daily dose should be calculated on the basis of 2 to 4 mg/lb/day (4.4 to 8.8 mg/kg/day), but not to exceed 150 mg per day.

9 yrs. to 12 yrs. of age

The total daily dose is 200 mg given as one tablet of 100 mg twice a day. The 100 mg daily dose has not been studied in this pediatric population. Therefore, there are no data which demonstrate that this dose is as effective as or is safer than the 200 mg daily dose in this patient population.

Prophylactic dosing should be started in anticipation of an influenza A outbreak and before or after contact with individuals with influenza A virus respiratory tract illness.

Amantadine hydrochloride tablets should be continued daily for at least 10 days following a known exposure. If amantadine hydrochloride tablets are used chemoprophylactically in conjunction with inactivated influenza A virus vaccine until protective antibody responses develop, then it should be administered for 2 to 4 weeks after the vaccine has been given. When inactivated influenza A virus vaccine is unavailable or contraindicated, amantadine hydrochloride tablets should be administered for the duration of known influenza A in the community because of repeated and unknown exposure.

Treatment of influenza A virus illness should be started as soon as possible, preferably within 24 to 48 hours after onset of signs and symptoms, and should be continued for 24 to 48 hours after the disappearance of signs and symptoms.

Dosage for Parkinsonism

Adult

The usual dose of amantadine hydrochloride tablet is 100 mg twice a day when used alone. Amantadine hydrochloride tablets have an onset of action usually within 48 hours.

The initial dose of amantadine hydrochloride tablet is 100 mg daily for patients with serious associated medical illnesses or who are receiving high doses of other antiparkinson drugs. After one to several weeks at 100 mg once daily, the dose may be increased to 100 mg twice daily, if necessary.

Occasionally, patients whose responses are not optimal with amantadine hydrochloride tablets at 200 mg daily may benefit from an increase up to 400 mg daily in divided doses. However, such patients should be supervised closely by their physicians.

Patients initially deriving benefit from amantadine hydrochloride tablets not uncommonly experience a fall-off of effectiveness after a few months. Benefit may be regained by increasing the dose to 300 mg daily. Alternatively, temporary discontinuation of amantadine hydrochloride tablets for several weeks, followed by reinitiation of the drug, may result in regaining benefit in some patients. A decision to use other antiparkinson drugs may be necessary.

Dosage for Concomitant Therapy

Some patients who do not respond to anticholinergic antiparkinson drugs may respond to amantadine hydrochloride tablets. When amantadine hydrochloride tablets or anticholinergic antiparkinson drugs are each used with marginal benefit, concomitant use may produce additional benefit.

When amantadine hydrochloride and levodopa are initiated concurrently, the patient can exhibit rapid therapeutic benefits. Amantadine hydrochloride should be held constant at 100 mg daily or twice daily while the daily dose of levodopa is gradually increased to optimal benefit.

When amantadine hydrochloride is added to optimal well-tolerated doses of levodopa, additional benefit may result, including smoothing out the fluctuations in improvement which sometimes occur in patients on levodopa alone. Patients who require a reduction in their usual dose of levodopa because of development of side effects may possibly regain lost benefit with the addition of amantadine hydrochloride.
Dosage for Drug-Induced Extrapyramidal Reactions

Adult

The usual dose of amantadine hydrochloride tablet is 100 mg twice a day. Occasionally, patients whose responses are not optimal with amantadine hydrochloride tablets at 200 mg daily may benefit from an increase up to 300 mg daily in divided doses.

Dosage for Impaired Renal Function

Depending upon creatinine clearance, the following dosage adjustments are recommended:

CREATININE CLEARANCE (mL/min/1.73 m^2) | AMANTADINE HYDROCHLORIDE TABLETS DOSAGE
30 to 50 | 200 mg 1st day and 100 mg each day thereafter
15 to 29 | 200 mg 1st day followed by 100 mg on alternate days
<15 | 200 mg every 7 days

The recommended dosage for patients on hemodialysis is 200 mg every 7 days.

HOW SUPPLIED

Amantadine hydrochloride tablets, USP are available as peach color, round, flat face, beveled-edge mottled tablets, debossed with ‘L 75’ on one side and plain on other side as follows:

Bottle of 20 tablets, NDC 82804-267-20

Store at 25°C (77°F), excursions permitted to 15° to 30°C (59° to 86°F) [see USP Controlled Room Temperature].

Dispense in a tight container as defined in the USP, with a child-resistant closure (as required).

REFERENCES

^1 W.W. Wilson and A.H. Rajput, Amantadine-Dyazide Interaction, Can. Med. Assoc. J. 129:974-975, 1983.

^2 D.F. Casey, N. Engl. J. Med. 298:516, 1978.

^3 C.D. Berkowitz, J. Pediatr. 95:144, 1979.

Brands listed are trademarks of their respective owners.
Manufactured by:

Alembic Pharmaceuticals Limited

(Formulation Division),

Panelav 389350, Gujarat, India

Manufactured for:

Alembic Pharmaceuticals, Inc.

Bedminster, NJ 07921, USA

Repackaged by:

Proficient Rx LP

Thousand Oaks, CA 91320

Revised: 06/2025

PACKAGE LABEL.PRINCIPAL DISPLAY PANEL - 100 mg

NDC 82804-267-20
Amantadine
Hydrochloride
Tablets, USP
100 mg
Rx only
20 Tablets